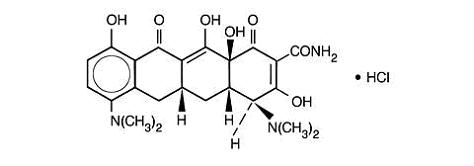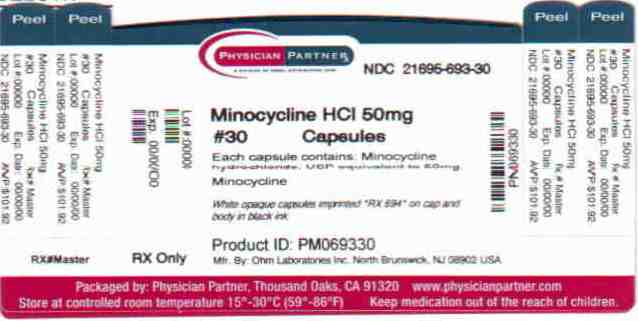 DRUG LABEL: Minocycline Hydrochloride
NDC: 21695-693 | Form: CAPSULE
Manufacturer: Rebel Distributors Corp.
Category: prescription | Type: HUMAN PRESCRIPTION DRUG LABEL
Date: 20101006

ACTIVE INGREDIENTS: minocycline hydrochloride 50 mg/1 1
INACTIVE INGREDIENTS: FERROSOFERRIC OXIDE; STARCH, CORN; gelatin; magnesium stearate; titanium dioxide

MINOCYCLINE HYDROCHLORIDE CAPSULES, USP
Rx only

To reduce the development of drug-resistant bacteria and maintain the effectiveness of minocycline hydrochloride capsules and other antibacterial drugs, minocycline hydrochloride capsules should be used only to treat or prevent infections that are proven or strongly suspected to be caused by bacteria.

DESCRIPTION

Minocycline hydrochloride, a semisynthetic derivative of tetracycline, is [4S-(4α,5aα,12aα)]-4,7- Bis(dimethylamino)-1,4,4a,5,5a,6,11,12a-octahydro-3,10,12,12a-tetrahydroxy-1,11-dioxo-2- naphthacenecarboxamide monohydrochloride. Its structural formula is represented below:

C23H27N3O7.HCl M.W. 493.95

Each Minocycline hydrochloride capsule, for oral administration, contains the equivalent of 50 mg, 75 mg or 100 mg of minocycline. In addition each capsule contains the following inactive ingredients: magnesium stearate and corn starch.

The 50 mg, 75 mg and 100 mg capsule shells contain: gelatin, titanium dioxide and black iron oxide in the edible ink.

The 75 mg and 100 mg capsule shells also contain: black iron oxide.

CLINICAL PHARMACOLOGY

Following oral administration of minocycline hydrochloride capsules, absorption from gastro-intestinal tract is rapid. Maximum serum concentrations following a single dose of minocycline hydrochloride to normal fasting adult volunteers were attained in 1 to 4 hours. The serum half-life in the normal volunteers ranges from 11 hours to 22 hours.

When minocycline hydrochloride capsules were given concomitantly with a meal, which included dairy products, the extent of absorption of minocycline hydrochloride capsules was not noticeably influenced. The peak plasma concentrations were slightly decreased (11.2%) and delayed by one hour when administered with food, compared to dosing under fasting conditions.

In previous studies with other minocycline dosage forms, the minocycline serum half-life ranged from 11 to 16 hours in 7 patients with hepatic dysfunction, and from 18 to 69 hours in 5 patients with renal dysfunction. The urinary and fecal recovery of minocycline when administered to 12 normal volunteers was one-half to one-third that of other tetracyclines.

Microbiology

The tetracyclines are primarily bacteriostatic and are thought to exert their antimicrobial effect by the inhibition of protein synthesis. The tetracyclines, including minocycline, have a similar antimicrobial spectra of activity against a wide range of gram-positive and gram-negative organisms. Cross-resistance of these organisms to tetracycline is common.

While in vitro studies have demonstrated the susceptibility of most strains of the following microorganisms, clinical efficacy for infections other than those included in the INDICATIONS AND USAGE section has not been documented.

GRAM-NEGATIVE MICROORGANISMS

Bartonella bacilliformis

Brucella species

Campylobacter fetus

Francisella tularensis

Haemophilus ducreyi

Listeria monocytogenes

Neisseria gonorrhoeae

Vibrio cholerae

Yersinia pestis

Because many strains of the following groups of gram-negative microorganisms have been shown to be resistant to tetracyclines, culture and susceptibility tests are especially recommended.

Acinetobacter species

Enterobacter

Enterobacter aerogenes

Escherichia coli

Haemophilus influenzae

Klebsiella species

Shigella species

Gram-Positive Bacteria

Because many strains of the following groups of gram-positive microorganisms have been shown to be resistant to tetracyclines, culture and susceptibility testing are especially recommended. Up to 44 percent of Streptococcus pyogenes strains have been found to be resistant to tetracycline drugs. Therefore, tetracyclines should not be used for streptococcal disease unless the organism has been demonstrated to be susceptible.

Alpha-hemolytic streptococci (viridans group)

Streptococcus pneumoniae

Streptococcus pyogenes

“OTHER” MICROORGANISMS

Actinomyces species

Bacillus anthracis

Balantidium coli

Borrelia recurrentis

Chlamydia psittaci

Chlamydia trachomatis

Clostridium species

Entamoeba species

Fusobacterium fusiforme

Propionibacterium acnes

Treponema pallidum

Treponema pertenue

Ureaplasma urealyticum

Susceptibility Tests

Diffusion Techniques:

The use of antibiotic disk susceptibility test methods which measure zone diameter gives an accurate estimation of susceptibility of microorganisms to minocycline. One such standard procedure^1 has been recommended for use with disks for testing antimicrobials. Either the 30 mcg tetracycline-class disk or the 30 mcg minocycline disk should be used for the determination of the susceptibility of microorganisms to minocycline. With this type of procedure a report of “susceptible” from the laboratory indicates that the infecting organism is likely to respond to therapy. A report of “intermediate susceptibility” suggests that the organism would be susceptible if a high dosage is used or if the infection is confined to tissues and fluids (e.g., urine) in which high antibiotic levels are attained. A report of “resistant” indicates that the infecting organism is not likely to respond to therapy. With either the tetracycline-class disk or the minocycline disk, zone sizes of 19 mm or greater indicate susceptibility, zone sizes of 14 mm or less indicate resistance, and zone sizes of 15 to 18 mm indicate intermediate susceptibility.

Standardized procedures require the use of laboratory control organisms. The 30 mcg tetracycline disk should give zone diameters between 19 and 28 mm for Staphylococcus aureus ATCC 25923 and between 18 and 25 mm for Escherichia coli ATCC 25922. The 30 mcg minocycline disk should give zone diameters between 25 and 30 mm for S. aureus ATCC 25923 and between 19 and 25 mm for E. coli ATCC 25922.

Dilution Techniques:

When using the NCCLS agar dilution or broth dilution (including microdilution) method^2 or equivalent, a bacterial isolate may be considered susceptible if the MIC (minimal inhibitory concentration) of minocycline is 4 mcg/mL or less. Organisms are considered resistant if the MIC is 16 mcg/mL or greater. Organisms with an MIC value of less than 16 mcg/mL but greater than 4 mcg/mL are expected to be susceptible if a high dosage is used or if the infection is confined to tissues and fluids (e.g., urine) in which high antibiotic levels are attained.

As with standard diffusion methods, dilution procedures require the use of laboratory control organisms. Standard tetracycline or minocycline powder should give MIC values of 0.25 mcg/mL to 1.0 mcg/mL for S. aureus ATCC 25923, and 1.0 mcg/mL to 4.0 mcg/mL for E. coli ATCC 25922.

INDICATIONS AND USAGE

To reduce the development of drug-resistant bacteria and maintain the effectiveness of minocycline hydrochloride capsules and other antibacterial drugs, minocycline hydrochloride capsules should be used only to treat or prevent infections that are proven or strongly suspected to be caused by susceptible bacteria. When culture and susceptibility information are available, they should be considered in selecting or modifying antibacterial therapy. In the absence of such data, local epidemiology and susceptibility patterns may contribute to the empiric selection of therapy.

Minocycline hydrochloride capsules are indicated in the treatment of the following infections due to susceptible strains of the designated microorganisms:

Rocky Mountain spotted fever, typhus fever and the typhus group, Q fever, rickettsialpox and tick fevers caused by Rickettsiae.

Respiratory tract infections caused by Mycoplasma pneumoniae.

Lymphogranuloma venereum caused by Chlamydia trachomatis.

Psittacosis (Ornithosis) due to Chlamydia psittaci.

Trachoma caused by Chlamydia trachomatis, although the infectious agent is not always eliminated, as judged by immunofluorescence.

Inclusion conjunctivitis caused by Chlamydia trachomatis.

Nongonococcal urethritis, in adults caused by Ureaplasma urealyticum or Chlamydia trachomatis.

Relapsing fever due to Borrelia recurrentis.

Chancroid caused by Haemophilus ducreyi.

Plague due to Yersinia pestis.

Tularemia due to Francisella tularensis.

Cholera caused by Vibrio cholerae.

Campylobacter fetus infections caused by Campylobacter fetus.

Brucellosis due to Brucella species (in conjunction with streptomycin).

Bartonellosis due to Bartonella bacilliformis.

Granuloma inguinale caused by Calymmatobacterium granulomatis.

Minocycline is indicated for the treatment of infections caused by the following gram-negative microorganisms when bacteriologic testing indicates appropriate susceptibility to the drug:

Escherichia coli.

Enterobacter aerogenes.

Shigella species.

Acinetobacter species.

Respiratory tract infections caused by Haemophilus influenzae.

Respiratory tract and urinary tract infections caused by Klebsiella species.

Minocycline hydrochloride capsules are indicated for the treatment of infections caused by the following gram-positive microorganisms when bacteriologic testing indicates appropriate susceptibility to the drug:

Upper respiratory tract infections caused by Streptococcus pneumoniae.

Skin and skin structure infections caused by Staphylococcus aureus. (Note: Minocycline is not the drug of choice in the treatment of any type of staphylococcal infection.)

Uncomplicated urethritis in men due to Neisseria gonorrhoeae and for the treatment of other gonococcal infections.

When penicillin is contraindicated, minocycline is an alternative drug in the treatment of the following infections:

Infections in women caused by Neisseria gonorrhoeae.

Syphilis caused by Treponema pallidum.

Yaws caused by Treponema pallidum.

Listeriosis due to Listeria monocytogenes.

Anthrax due to Bacillus anthracis.

Vincent’s infection caused by Fusobacterium fusiforme.

Actinomycosis caused by Actinomyces israelii.

Infections caused by Clostridium species.

In acute intestinal amebiasis, minocycline may be a useful adjunct to amebicides.

In severe acne, minocycline may be useful adjunctive therapy.

Oral minocycline is indicated in the treatment of asymptomatic carriers of Neisseria meningitidis to eliminate meningococci from the nasopharynx. In order to preserve the usefulness of minocycline in the treatment of asymptomatic meningococcal carriers, diagnostic laboratory procedures, including serotyping and susceptibility testing, should be performed to establish the carrier state and the correct treatment. It is recommended that the prophylactic use of minocycline be reserved for situations in which the risk of meningococcal meningitis is high.

Oral minocycline is not indicated for the treatment of meningococcal infection.

Although no controlled clinical efficacy studies have been conducted, limited clinical data show that oral minocycline hydrochloride has been used successfully in the treatment of infections caused by Mycobacterium marinum.

CONTRAINDICATIONS

This drug is contraindicated in persons who have shown hypersensitivity to any of the tetracyclines.

WARNINGS

MINOCYCLINE, LIKE OTHER TETRACYCLINE-CLASS ANTIBIOTICS, CAN CAUSE FETAL HARM WHEN ADMINISTERED TO A PREGNANT WOMAN. IF ANY TETRACYCLINE IS USED DURING PREGNANCY OR IF THE PATIENT BECOMES PREGNANT WHILE TAKING THESE DRUGS, THE PATIENT SHOULD BE APPRISED OF THE POTENTIAL HAZARD TO THE FETUS. THE USE OF DRUGS OF THE TETRACYCLINE CLASS DURING TOOTH DEVELOPMENT (LAST HALF OF PREGNANCY, INFANCY, AND CHILDHOOD TO THE AGE OF 8 YEARS) MAY CAUSE PERMANENT DISCOLORATION OF THE TEETH (YELLOW-GRAY-BROWN).

This adverse reaction is more common during long-term use of the drug but has been observed following repeated short-term courses. Enamel hypoplasia has also been reported. TETRACYCLINE DRUGS, THEREFORE, SHOULD NOT BE USED DURING TOOTH DEVELOPMENT UNLESS OTHER DRUGS ARE NOT LIKELY TO BE EFFECTIVE OR ARE CONTRAINDICATED.

All tetracyclines form a stable calcium complex in any bone-forming tissue. A decrease in the fibula growth rate has been observed in young animals (rats and rabbits) given oral tetracycline in doses of 25 mg/kg every six hours. This reaction was shown to be reversible when the drug was discontinued.

Results of animal studies indicate that tetracyclines cross the placenta, are found in fetal tissues, and can have toxic effects on the developing fetus (often related to retardation of skeletal development). Evidence of embryotoxicity has been noted in animals treated early in pregnancy.

The anti-anabolic action of the tetracyclines may cause an increase in BUN. While this is not a problem in those with normal renal function, in patients with significantly impaired function, higher serum levels of tetracycline may lead to azotemia, hyperphosphatemia, and acidosis. If renal impairment exists, even usual oral or parenteral doses may lead to excessive systemic accumulations of the drug and possible liver toxicity. Under such conditions, lower than usual total doses are indicated, and if therapy is prolonged, serum level determinations of the drug may be advisable.

Photosensitivity manifested by an exaggerated sunburn reaction has been observed in some individuals taking tetracyclines. This has been reported with minocycline.

Central nervous system side effects including light-headedness, dizziness, or vertigo have been reported with minocycline therapy. Patients who experience these symptoms should be cautioned about driving vehicles or using hazardous machinery while on minocycline therapy. These symptoms may disappear during therapy and usually disappear rapidly when the drug is discontinued.

PRECAUTIONS

General

Prescribing Minocycline hydrochloride capsules in the absence of a proven or strongly suspected bacterial infection or a prophylactic indication is unlikely to provide benefit to the patient and increases the risk of the development of drug-resistant bacteria.

As with other antibiotic preparations, use of this drug may result in overgrowth of non-susceptible organisms, including fungi. If superinfection occurs, the antibiotic should be discontinued and appropriate therapy instituted.

Pseudotumor cerebri (benign intracranial hypertension) in adults has been associated with the use of tetracyclines. The usual clinical manifestations are headache and blurred vision. Bulging fontanels have been associated with the use of tetracyclines in infants. While both of these conditions and related symptoms usually resolve after discontinuation of the tetracycline, the possibility for permanent sequelae exists.

Incision and drainage or other surgical procedures should be performed in conjunction with antibiotic therapy when indicated.

Information for Patients

Patients should be counseled that antibacterial drugs including minocycline hydrochloride capsules should only be used to treat bacterial infections. They do not treat viral infections (e.g., the common cold). When minocycline hydrochloride capsules are prescribed to treat a bacterial infection, patients should be told that although it is common to feel better early in the course of therapy, the medication should be taken exactly as directed. Skipping doses or not completing the full course of therapy may (1) decrease the effectiveness of the immediate treatment and (2) increase the likelihood that bacteria will develop resistance and will not be treatable by minocycline hydrochloride capsules or other antibacterial drugs in the future.

Photosensitivity manifested by an exaggerated sunburn reaction has been observed in some individuals taking tetracyclines. Patients apt to be exposed to direct sunlight or ultraviolet light should be advised that this reaction can occur with tetracycline drugs, and treatment should be discontinued at the first evidence of skin erythema. This reaction has been reported with use of minocycline.

Patients who experience central nervous system symptoms (See WARNINGS.) should be cautioned about driving vehicles or using hazardous machinery while on minocycline therapy.

Concurrent use of tetracycline may render oral contraceptives less effective. (See Drug Interactions.)

Laboratory Tests

In venereal disease when coexistent syphilis is suspected, a dark-field examination should be done before treatment is started and the blood serology repeated monthly for at least four months.

In long term therapy, periodic laboratory evaluations of organ systems, including hematopoietic, renal, and hepatic studies should be performed.

Drug Interactions

Because tetracyclines have been shown to depress plasma prothrombin activity, patients who are on anticoagulant therapy may require downward adjustment of their anticoagulant dosage.

Since bacteriostatic drugs may interfere with the bactericidal action of penicillin, it is advisable to avoid giving tetracycline-class drugs in conjunction with penicillin.

Absorption of tetracyclines is impaired by antacids containing aluminum, calcium, or magnesium, and iron-containing preparations.

The concurrent use of tetracycline and methoxyflurane has been reported to result in fatal renal toxicity.

Concurrent use of tetracyclines with oral contraceptives may render oral contraceptives less effective.

Drug / Laboratory Test Interactions

False elevations of urinary catecholamine levels may occur due to interference with the fluorescence test.

Carcinogenesis, Mutagenesis, Impairment of Fertility

Dietary administration of minocycline in long term tumorigenicity studies in rats resulted in evidence of thyroid tumor production. Minocycline has also been found to produce thyroid hyperplasia in rats and dogs. In addition, there has been evidence of oncogenic activity in rats in studies with a related antibiotic, oxytetracycline (i.e., adrenal and pituitary tumors). Likewise, although mutagenicity studies of minocycline have not been conducted, positive results in in vitro mammalian cell assays (i.e., mouse lymphoma and Chinese hamster lung cells) have been reported for related antibiotics (tetracycline hydrochloride and oxytetracycline). Segment I (fertility and general reproduction) studies have provided evidence that minocycline impairs fertility in male rats.

Teratogenic Effects:

Pregnancy

Pregnancy Category D. (See WARNINGS.)

Labor and Delivery

The effect of tetracyclines on labor and delivery is unknown.

Nursing Mothers

Tetracyclines are excreted in human milk. Because of the potential for serious adverse reactions in nursing infants from the tetracyclines, a decision should be made whether to discontinue nursing or discontinue the drug, taking into account the importance of the drug to the mother. (See WARNINGS.)

Pediatric Use

(See WARNINGS.)

ADVERSE REACTIONS

Due to oral minocycline’s virtually complete absorption, side effects to the lower bowel, particularly diarrhea, have been infrequent. The following adverse reactions have been observed in patients receiving tetracyclines.

Gastrointestinal: Anorexia, nausea, vomiting, diarrhea, glossitis, dysphagia, enterocolitis, pancreatitis, inflammatory lesions (with monilial over growth) in anogenital region, and increases in liver enzymes. Rarely, hepatitis and liver failure have been reported. Rare instances of esophagitis and esophageal ulcerations have been reported in patients taking the tetracycline-class antibiotics in capsule and tablet form. Most of these patients took the medication immediately before going to bed (see DOSAGE AND ADMINISTRATION)

Skin: Maculopapular and erythematous rashes. Exfoliative dermatitis has been reported but is uncommon. Fixed drug eruptions, including balanitis, have been rarely reported. Erythema multiforme and rarely Stevens-Johnson syndrome have been reported. Photosensitivity is discussed above (see WARNINGS). Pigmentation of the skin and mucous membranes has been reported.

Renal toxicity: Elevations in BUN have been reported and are apparently dose related (see WARNINGS).

Hypersensitivity reactions:

Urticaria, angioneurotic edema, polyarthralgia, anaphylaxis, anaphylactoid purpura, pericarditis, exacerbation of systemic lupus erythematosus and rarely pulmonary infiltrates with eosinophilia have been reported. A transient lupus-like syndrome has also been reported.

Blood: Hemolytic anemia, thrombocytopenia, neutropenia, and eosinophilia have been reported.

Central Nervous System: Bulging fontanels in infants and benign intracranial hypertension (Pseudotumor cerebri) in adults (see PRECAUTIONS - General) have been reported. Headache has also been reported.

Other: When given over prolonged periods, tetracyclines have been reported to produce brown-black microscopic discoloration of the thyroid glands. Very rare cases of abnormal thyroid function have been reported.

Decreased hearing has been rarely reported in patients on minocycline hydrochloride.

Tooth discoloration in children less than 8 years of age (see WARNINGS) and also, rarely, in adults has been reported.

OVERDOSAGE

In case of overdosage, discontinue medication, treat symptomatically, and institute supportive measures.

DOSAGE AND ADMINISTRATION

THE USUAL DOSAGE AND FREQUENCY OF ADMINISTRATION OF MINOCYCLINE DIFFERS FROM THAT OF THE OTHER TETRACYCLINES. EXCEEDING THE RECOMMENDED DOSAGE MAY RESULT IN AN INCREASED INCIDENCE OF SIDE EFFECTS.

Minocycline hydrochloride capsules may be taken with or without food (See CLINICAL PHARMACOLOGY.)

Adults

The usual dosage of minocycline hydrochloride capsules is 200 mg initially followed by 100 mg every 12 hours. Alternatively, if more frequent doses are preferred, two or four 50 mg capsules may be given initially followed by one 50 mg capsule four times daily.

For children Above 8 Years Of Age

The usual dose of minocycline hydrochloride capsules is 4 mg/kg initially followed by 2 mg/kg every 12 hours.

Uncomplicated gonococcal infections other than urethritis and anorectal infections in men: 200 mg initially, followed by 100 mg every 12 hours for a minimum of 4 days, with post-therapy cultures within 2 to 3 days.

In the treatment of uncomplicated gonococcal urethritis in men, 100 mg every 12 hours for five days is recommended.

For the treatment of syphilis, the usual dosage of minocycline hydrochloride should be administered over a period of 10 to 15 days. Close follow-up, including laboratory tests, is recommended.

In the treatment of meningococcal carrier state, the recommended dosage is 100 mg every 12 hours for five days.

Mycobacterium marinum infections: Although optimal doses have not been established, 100 mg every 12 hours for 6 to 8 weeks have been used successfully in a limited number of cases.

Uncomplicated urethral, endocervical, or rectal infection in adults caused by Chlamydiatrachomatis or Ureaplasma urealyticum: 100 mg orally, every 12 hours for at least 7 days.

Ingestion of adequate amounts of fluids along with capsule and tablet forms of drugs in the tetracycline-class is recommended to reduce the risk of esophageal irritation and ulceration.

In patients with renal impairment (see WARNINGS), the total dosage should be decreased by either reducing the recommended individual doses and/or by extending the time intervals between doses.

HOW SUPPLIED

Minocycline Hydrochloride Capsules, USP equivalent to 50 mg minocycline are white opaque capsules imprinted “Rx 694” on cap and body in black ink and supplied as follows:

Bottles of 30 NDC 21695-693-30

Store at 20 - 25° C (68 - 77° F). (See Controlled Room Temperature).

Protect from light, moisture, and excessive heat.

Dispense in a tight, light-resistant container as defined in the USP.

ANIMAL PHARMACOLOGY AND TOXICOLOGY

Minocycline hydrochloride has been observed to cause a dark discoloration of the thyroid in experimental animals (rats, minipigs, dogs, and monkeys). In the rat, chronic treatment with minocycline hydrochloride has resulted in goiter accompanied by elevated radioactive iodine uptake and evidence of thyroid tumor production. Minocycline hydrochloride has also been found to produce thyroid hyperplasia in rats and dogs.

REFERENCES

1. National Committee for Clinical Laboratory Standards, Approved Standard: Performance Standards for Antimicrobial Disk Susceptibility Tests, 3rd Edition, Vol. 4(16):M2-A3, Villanova, PA, December 1984.

2. National Committee for Clinical Laboratory Standards, Approved Standard: Methods for Dilution Antimicrobial Susceptibility Tests for Bacteria that Grow Aerobically, 2nd Edition, Vol. 5(22):M7-A, Villanova, PA, December 1985.

Manufactured for:

Ranbaxy Pharmaceuticals Inc.

Jacksonville, FL 32216 USA

By: Ohm Laboratories, Inc.

North Brunswick, NJ 08902 USA

April 2007

Repackaged by:

Rebel Distributors Corp

Thousand Oaks, CA 91320